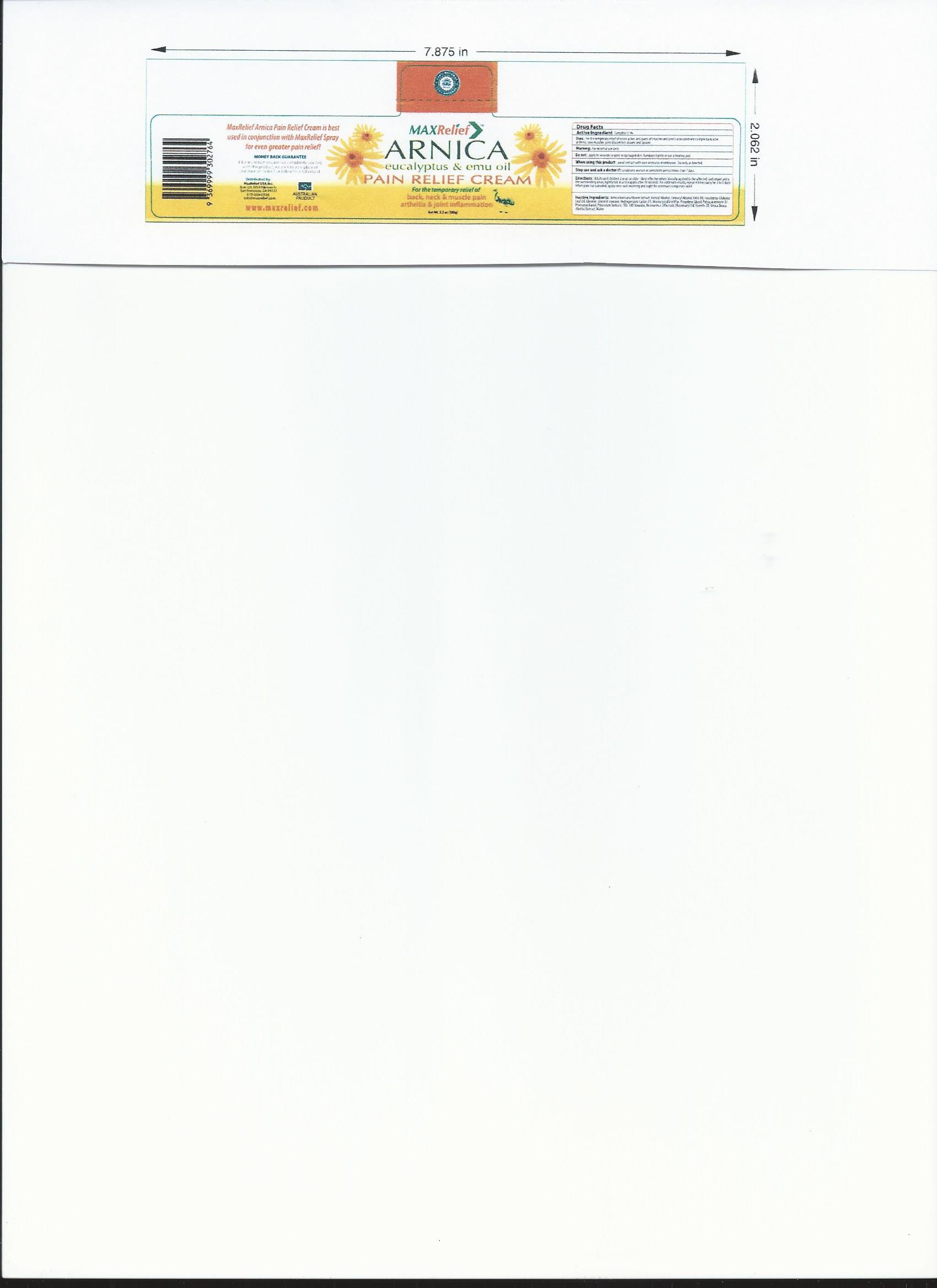 DRUG LABEL: MaxRelief Arnica
                
NDC: 76509-700 | Form: CREAM
Manufacturer: Natures Investment Holdings Pty Ltd dba Maxrelief USA
Category: otc | Type: HUMAN OTC DRUG LABEL
Date: 20160813

ACTIVE INGREDIENTS: CAMPHOR (NATURAL) 30 mg/1000 mg
INACTIVE INGREDIENTS: ARNICA MONTANA FLOWER; ROSEMARY OIL; EUCALYPTUS OIL; EMU OIL; ALCOHOL; WATER

Drug Facts

Inactive Ingredients: 100% Natural Arnica Montana Flower

Tincture, Rosemary Oil, Eucalyptus Oil. Also contains Emu Oil.

Ethanol and Water.

Active Ingredient Camphor .3 % Minimum Content

Purpose External Analgesic

INDICATIONS AND USAGE

Use - For the temporary relief of minor aches and pains associated with sore

muscles, joint discomfort, strains, sprains and arthritis.

WARNINGS

Warning: External use only.

When using this product: Avoid contact with eyes - Do not use on wounds, damaged

or irritated skin - Do not bandage, or use with heating pads or heating devices,

other ointments, creams, sprays or liniments.

Stop use and consult a doctor if: condition worsens - symptoms persist for

more than 7 days - symptoms clear up and reoccur

Keep out of reach of children: If swallowed, get medical help or

contact a Poison Control Center immediately

DOSAGE AND ADMINISTRATION

Directions: Adults and children 2 years of age or older: Most effective

when liberally applied to the affected, and importantly, the surrounding, areas.

Lightly rub in and reapply after 30 seconds. For optimum results, repeat 4 times

daily for 3 to 5 days. When the pain has subsided, apply once each

morning and evening for continued temporary relief.